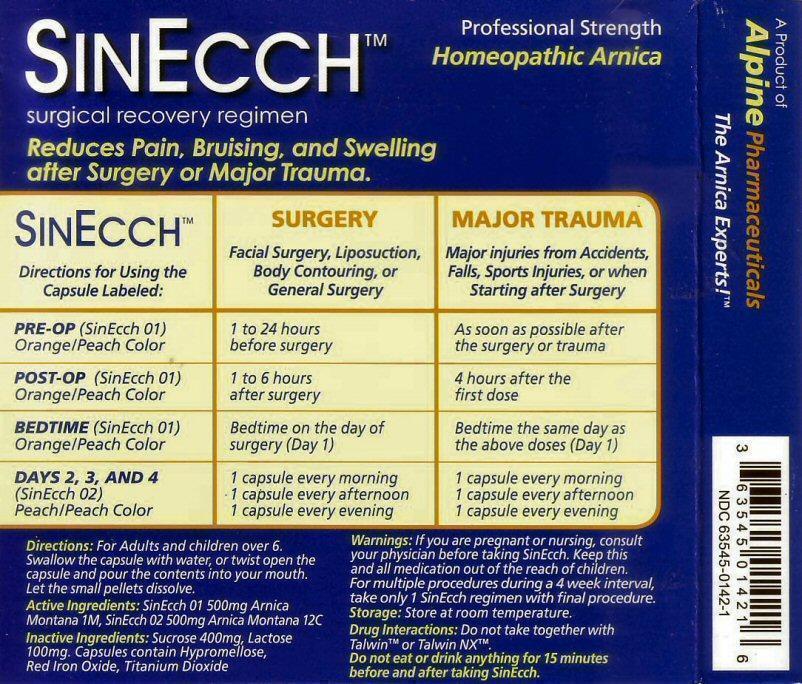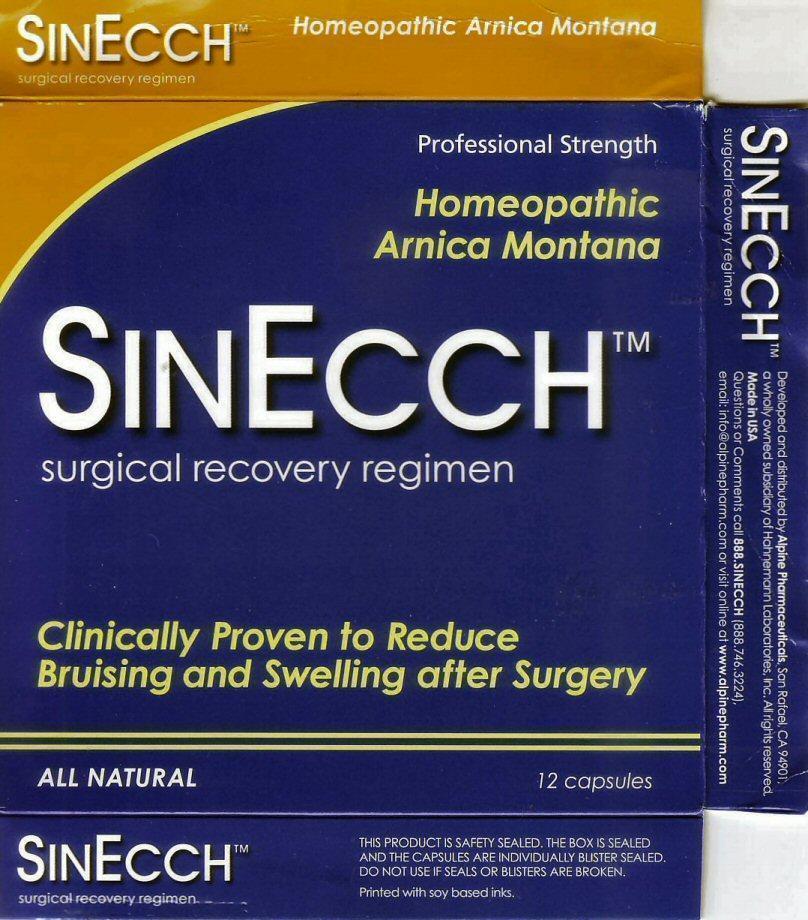 DRUG LABEL: SINECCH
NDC: 63545-142 | Form: CAPSULE
Manufacturer: Hahnemann Laboratories, Inc. dba Alpine Pharmaceuticals
Category: homeopathic | Type: HUMAN OTC DRUG LABEL
Date: 20150921

ACTIVE INGREDIENTS: ARNICA MONTANA 1 [hp_M]/1 1
INACTIVE INGREDIENTS: SUCROSE; LACTOSE; HYPROMELLOSES; FERRIC OXIDE RED; TITANIUM DIOXIDE

Active Ingredient

Active Ingredients: SinEcch 01 500mg Arnica Montana 1M, SinEcch 02 500mg Arnica Montana 12C

Purpose

surgical recovery regimen
Reduces Pain, Bruising, and Swelling after Surgery or Major Trauma.

Keep Out of Reach of Children

Keep this and all medication out of the reach of children.

Uses

Surgery or Major Trauma

Warnings

Warnings: If you are pregnant or nursing, consult your physician before taking SinEcch. For multiple procedures during a 4 week interval, take only 1 SinEcch regimen with the final procedure.
Do not drink or eat anything for 15 minutes before and after taking SinEcch.

Drug Interactions

Drug Interactions: Do not take together with Talwin tm or Talwin NX tm

Storage

Storage: Store at room temperature.

Directions

Directions: For Adults and children over 6. Swallow the capsule with water, or twist open the capsule and pour contents into your mouth. Let the small pellets dissolve.
SinEcch SURGERY MAJOR TRAUMA
Directions for Using the Facial Surgery, Liposuction, Major injuries from Accidents,
Capsule Labeled: Body Contouring, or Falls, Sports Injuries, or when
General Surgery Starting after Surgery
___________________________________________________________________________________
PRE-OP (SinEcch 01 1-24 hours As soon as possible after
Orange/Peach Color before surgery the surgery or trauma
___________________________________________________________________________________
POST-OP (SinEcch 01) 1-6 hours 4 hours after the
Orange/Peach Color after surgery first dose
__________________________________________________________________________________
BEDTIME (SinEcch 01) Bedtime on the day of Bedtime the same day as
Orange/Peach Color surgery (Day 1) the above doses (Day 1)
__________________________________________________________________________________
DAYS 2, 3, AND 4 1 capsule every morning 1 capsule every morning
(SinEcch 02) 1 capsule every afternoon 1 capsule every afternoon
Peach/Peach Color 1 capsule every evening 1 capsule every evening
__________________________________________________________________________________

Inactive Ingredients

Inactive Ingredients : Sucrose 400mg, Lactose 100 mg, Capsules contain Hypromellose, Red Iron Oxide, Titanium Dioxide

Package Label

SinEcch tm Homeopathic Arnica Montanan
surgical recovery regimen Professional Strength
Clinically Proven to Reduce Bruising and Swelling after Surgery
ALL NATURAL 12 capsules THIS PRODUCT IS SAFETY SEALED. THE BOX IS SEALED AND THE CAPSULES ARE INDIVIDUALLY BLISTER SEALED. DO NOT USE IF SEALS ARE BROKEN.
Printed with soy based inks.
Developed and distributed by Alpine Pharmaceuticals, San Rafael, CA 94901 a wholly owned subsidiary of Hahnemann Laboratories, Inc. All rights reserved. Made in the USA
Questions or comments call 888.SINECCH (888-746-3224) email: info@alpinepharm.com or visit online at www.alpinepharma.com
A Product of Alpine Pharmaceuticals The Arnica Experts! tm